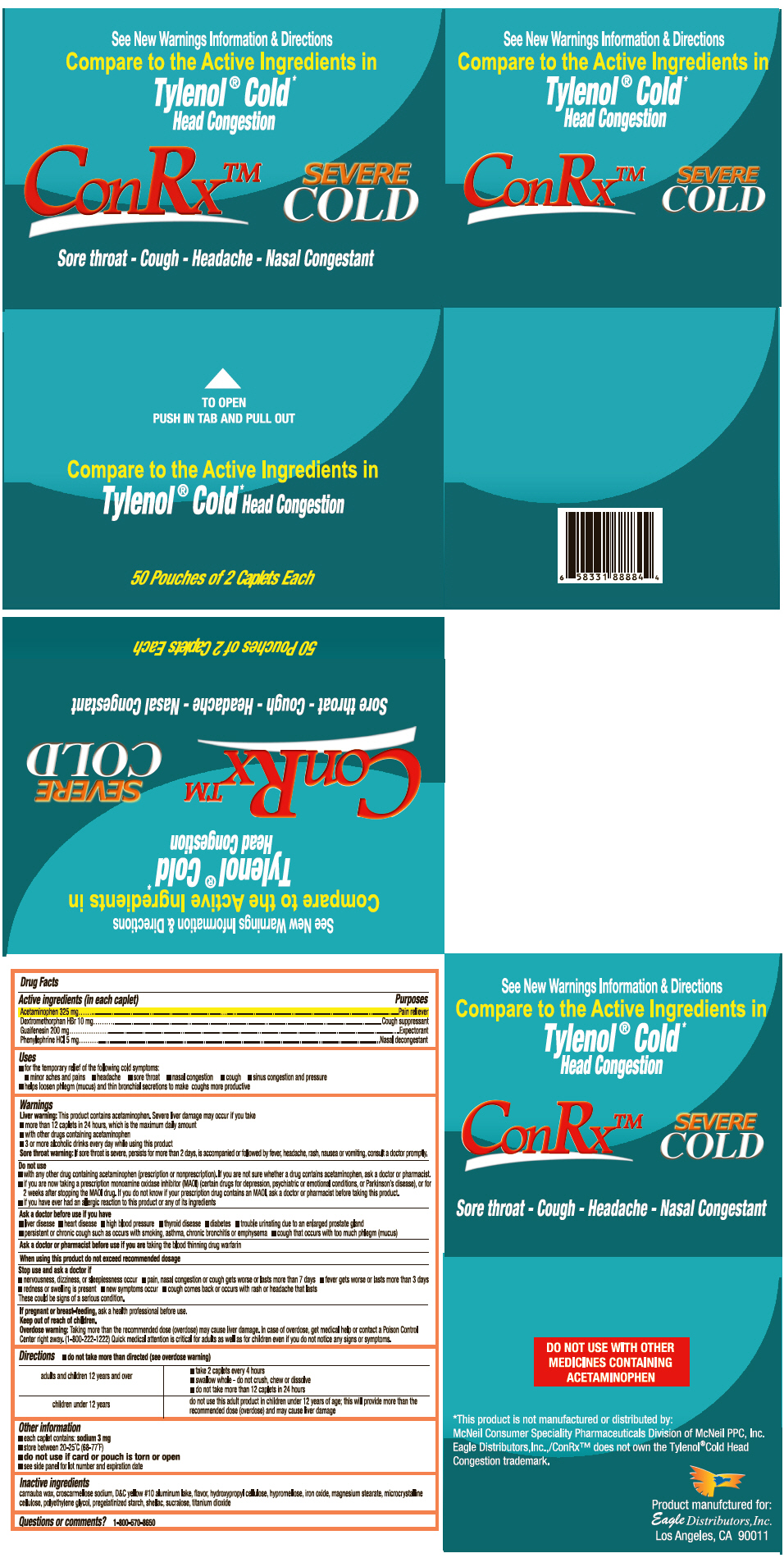 DRUG LABEL: ConRx Cold
NDC: 68737-232 | Form: TABLET
Manufacturer: Eagle Distributors,Inc.
Category: otc | Type: HUMAN OTC DRUG LABEL
Date: 20130212

ACTIVE INGREDIENTS: Acetaminophen 325 mg/1 1; Dextromethorphan Hydrobromide 10 mg/1 1; Guaifenesin 200 mg/1 1; Phenylephrine Hydrochloride 5 mg/1 1
INACTIVE INGREDIENTS: SILICON DIOXIDE; SODIUM LAURYL SULFATE; EDETATE DISODIUM; DOCUSATE SODIUM; STARCH, CORN; POVIDONE K90; GELATIN; MAGNESIUM STEARATE; CELLULOSE, MICROCRYSTALLINE; POLYETHYLENE GLYCOL 6000; SODIUM BENZOATE; SODIUM STARCH GLYCOLATE TYPE A CORN; STEARIC ACID; TALC; D&C YELLOW NO. 10; ALUMINUM OXIDE; TITANIUM DIOXIDE

ConRx™ Cold

Drug Facts

ACTIVE INGREDIENT

PURPOSE

Active ingredients(in each caplet) | Purposes
Acetaminophen 325 mg | Pain reliever
Dextromethorphan HBr 10 mg | Cough suppressant
Guaifenesin 200 mg | Expectorant
Phenylephrine HCl 5 mg | Nasal decongestant

Uses

- for the temporary relief of the following cold symptoms:
  - minor aches and pains
  - headache
  - sore throat
  - nasal congestion
  - cough
  - sinus congestion and pressure
- helps loosen phlegm (mucus) and thin bronchial secretions to make coughs more productive

Warnings

Liver warning

This product contains acetaminophen. Severe liver damage may occur if you take

- more than 12 caplets in 24 hours, which is the maximum daily amount
- with other drugs containing acetaminophen
- 3 or more alcoholic drinks every day while using this product.

Sore throat warning

If sore throat is severe, persists for more than 2 days, is accompanied or followed by fever, headache, rash, nausea or vomiting, consult a doctor promptly.

Do not use

- with any other drug containing acetaminophen (prescription or nonprescription). If you are not sure whether a drug contains acetaminophen, ask a doctor or pharmacist.
- if you are now taking a prescription monoamine oxidase inhibitor (MAOI) (certain drugs for depression, psychiatric or emotional conditions, or Parkinson's disease), or for 2 weeks after stopping the MAOI drug. If you do not know if your prescription drug contains an MAOI, ask a doctor or pharmacist before taking this product.
- if you have ever had an allergic reaction to this product or any of its ingredients

Ask a doctor before use if you have

- liver disease
- heart disease
- high blood pressure
- thyroid disease
- diabetes
- trouble urinating due to an enlarged prostate gland
- persistent or chronic cough such as occurs with smoking, asthma, chronic bronchitis or emphysema
- cough that occurs with too much phlegm (mucus)

Ask a doctor or pharmacist before use if you are taking the blood thinning drug warfarin

When using this product do not exceed recommended dosage

Stop use and ask a doctor if

- nervousness, dizziness, or sleeplessness occur
- pain, nasal congestion or cough gets worse or lasts more than 7 days
- fever gets worse or lasts more than 3 days
- redness or swelling is present
- new symptoms occur
- cough comes back or occurs with rash or headache that lasts.

These could be signs of a serious condition.

PREGNANCY OR BREAST FEEDING

If pregnant or breast-feeding, ask a health professional before use.

Keep out of reach of children.

Overdose warning

Taking more than the recommended dose (overdose) may cause liver damage. In case of overdose, get medical help or contact a Poison Control Center right away. (1-800-222-1222) Quick medical attention is critical for adults as well as for children even if you do not notice any signs or symptoms.

Directions

• do not take more than directed (see overdose warning)

adults and children 12 years and over

- take 2 caplets every 4 hours
- swallow whole - do not crush, chew or dissolve
- do not take more than 12 caplets in 24 hours

children under 12 years

- do not use this adult product in children under 12 years of age; this will provide more than the recommended dose (overdose) and may cause liver damage

Other information

- each caplet contains: sodium 3 mg
- store between 20-25°C (68-77°F)
- do not use if card or pouch is torn or open
- see side panel for lot number and expiration date

Inactive ingredients

carnauba wax, croscarmellose sodium, D&C yellow #10 aluminum lake, ﬂavor, hydroxypropyl cellulose, hypromellose, iron oxide, magnesium stearate, microcrystalline cellulose, polyethylene glycol, pregelatinized starch, shellac, sucralose, titanium dioxide

Questions or comments?

1-800-570-8650

PRINCIPAL DISPLAY PANEL - 50 Pouch Box

See New Warnings Information & Directions

Compare to the Active Ingredients in

Tylenol® Cold*
Head Congestion

ConRx™
SEVERE
COLD

Sore throat - Cough - Headache - Nasal Congestant

TO OPEN
PUSH IN TAB AND PULL OUT

Compare to the Active Ingredients in

Tylenol® Cold* Head Congestion

50 Pouches of 2 Caplets Each